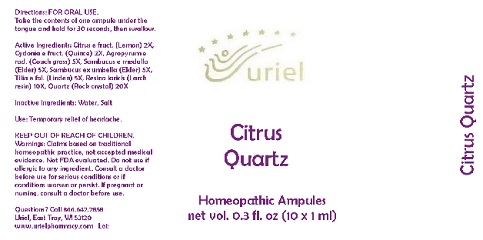 DRUG LABEL: Citrus Quartz
NDC: 48951-3107 | Form: LIQUID
Manufacturer: Uriel Pharmacy Inc.
Category: homeopathic | Type: HUMAN OTC DRUG LABEL
Date: 20180522

ACTIVE INGREDIENTS: LEMON 2 [hp_X]/1 mL; QUINCE 2 [hp_X]/1 mL; AGROPYRON FRAGILE WHOLE 5 [hp_X]/1 mL; SAMBUCUS CANADENSIS FLOWER 5 [hp_X]/1 mL; TILIA AMERICANA FLOWER 5 [hp_X]/1 mL; LARIX DECIDUA RESIN 10 [hp_X]/1 mL; SILICON DIOXIDE 20 [hp_X]/1 mL
INACTIVE INGREDIENTS: WATER; SODIUM CHLORIDE

Citrus Quartz

INDICATIONS AND USAGE

Directions: FOR ORAL USE ONLY.

DOSAGE AND ADMINISTRATION

Take the contents of one ampule
under the tongue and hold for
30 seconds, then swallow.

ACTIVE INGREDIENT

Active Ingredients: Citrus e fruct. (Lemon) 2X, Cydonia e fruct. (Quince) 2X,
Agropyrum e rad. (Couch grass) 5X, Sambucus
e medulla (Elder) 5X, Sambucus ex
umbella (Elder) 5X, Tilia e fol. (Linden) 5X,
Resina laricis (Larch resin) 10X, Quartz (Rock crystal) 20X

Inactive Ingredients: Water, Salt

PURPOSE

Use: Temporary relief of headache.

KEEP OUT OF REACH OF CHILDREN.

WARNINGS

Warnings: Claims based on traditional homeopathic practice, not accepted medical evidence. Not FDA evaluated. Do not use if allergic to any ingredient. Consult a doctor before use for serious conditions or if conditions worsen or persist. If pregnant or nursing, consult a doctor before use.

Questions? Call 866.642.2858
Uriel, East Troy, WI 53120
www.urielpharmacy.com